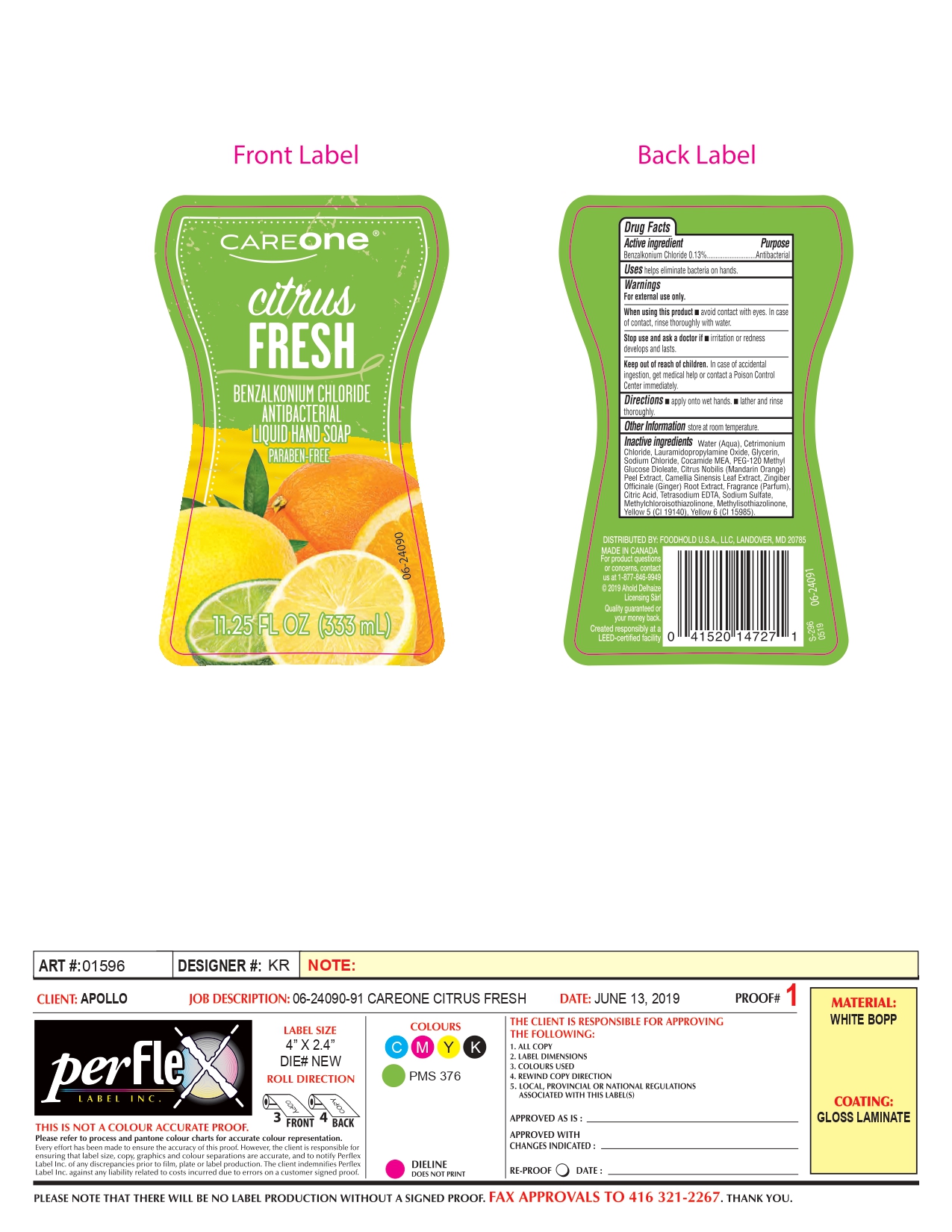 DRUG LABEL: Careone
NDC: 72476-003 | Form: SOAP
Manufacturer: Retail Business Services, LLC
Category: otc | Type: HUMAN OTC DRUG LABEL
Date: 20210902

ACTIVE INGREDIENTS: BENZALKONIUM CHLORIDE 130 mg/100 mL
INACTIVE INGREDIENTS: GLYCERIN; CETRIMONIUM CHLORIDE; CITRIC ACID MONOHYDRATE; METHYLISOTHIAZOLINONE; BASIC YELLOW 5; LAURAMIDOPROPYLAMINE OXIDE; SODIUM CHLORIDE; CITRUS NOBILIS; CAMELLIA SINENSIS FLOWER; COCO MONOETHANOLAMIDE; PEG-120 METHYL GLUCOSE DIOLEATE; ZINGIBER OFFICINALE WHOLE; FRAGRANCE FRESH CITRUS FLORAL ORC1501495; SODIUM SULFATE; DIRECT YELLOW 6; WATER; EDETATE SODIUM; METHYLCHLOROISOTHIAZOLINONE

Drug Facts

Active Ingredient

Benzalkonium Chloride (0.13%)

Purpose

Antibacterial

Uses

Helps eliminate bacteria on hands.

Warnings

For external use only.

When using this Product

- Avoid contact with eyes. In case of contact, rinse thoroughly with water.

Stop use and ask a doctor if

- irritation or redness develops and lasts.

Keep out of reach of children

In case of accidental ingestion, get medical help or contact a Poison Control Center immediately.

Directions

- Apply onto wet hands.
- Lather and rinse thoroughly..

Other Information

Store at Room Temperature

Inactive Ingredients

Water (Aqua), Cetrimonium Chloride, Lauramidopropylamine Oxide, Glycerin, Sodium Chloride, Cocamide MEA, PEG-120 Methyl Glucose Dioleate, Citrus Nobilis (Mandarin Orange) Peel Extract, Camellia Sinensis Leaf Extract, Zingiber Officinale (Ginger) Root Extract, Fragrance (Parfum), Citric Acid, Tetrasodium EDTA, Sodium Sulfate, Methylchloroisothiazolinone, Methylisothiazolinone, Yellow 5 (Cl 19140), Yellow 6 (Cl 15985).